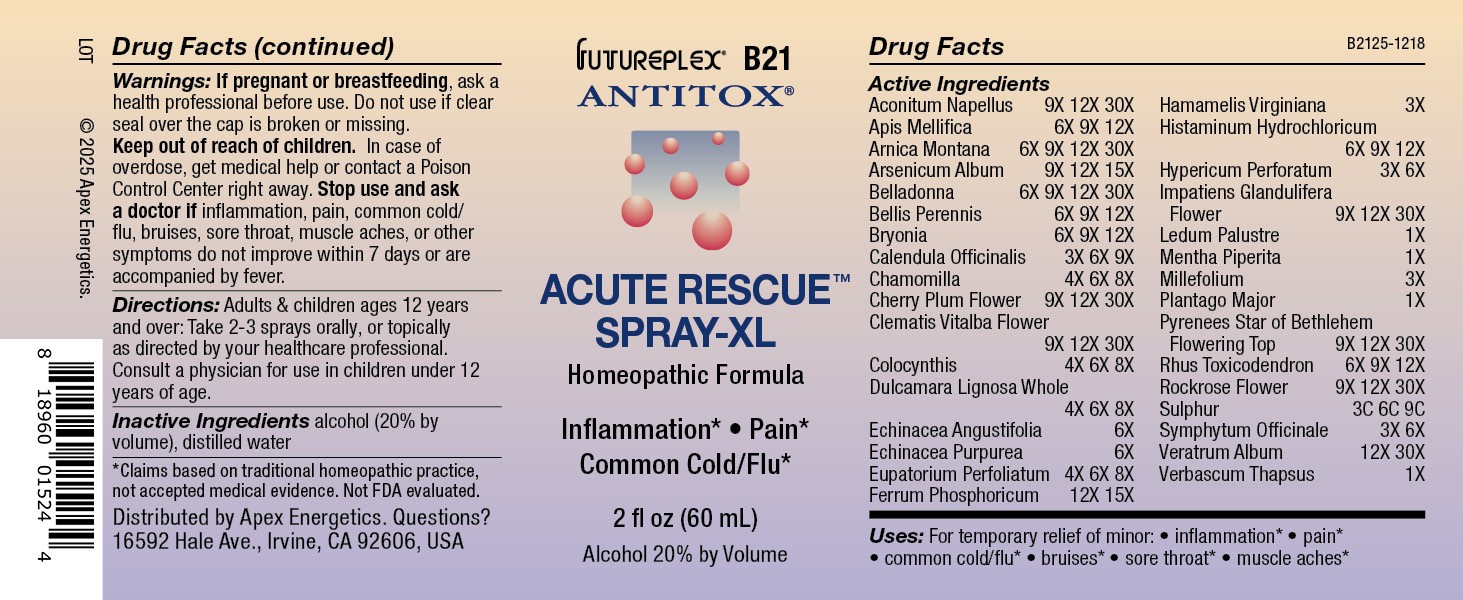 DRUG LABEL: B21
NDC: 63479-0221 | Form: SPRAY
Manufacturer: Apex Energetics Inc.
Category: homeopathic | Type: HUMAN OTC DRUG LABEL
Date: 20251231

ACTIVE INGREDIENTS: APIS MELLIFERA 12 [hp_X]/1 mL; ARNICA MONTANA 30 [hp_X]/1 mL; ATROPA BELLADONNA 30 [hp_X]/1 mL; BRYONIA ALBA ROOT 12 [hp_X]/1 mL; PRUNUS CERASIFERA FLOWER 30 [hp_X]/1 mL; CITRULLUS COLOCYNTHIS FRUIT PULP 8 [hp_X]/1 mL; ECHINACEA PURPUREA 6 [hp_X]/1 mL; ECHINACEA ANGUSTIFOLIA 6 [hp_X]/1 mL; LEDUM PALUSTRE TWIG 1 [hp_X]/1 mL; MENTHA PIPERITA 1 [hp_X]/1 mL; PLANTAGO MAJOR 1 [hp_X]/1 mL; ORNITHOGALUM UMBELLATUM FLOWERING TOP 30 [hp_X]/1 mL; TOXICODENDRON PUBESCENS LEAF 12 [hp_X]/1 mL; HELIANTHEMUM NUMMULARIUM FLOWER 30 [hp_X]/1 mL; HISTAMINE DIHYDROCHLORIDE 12 [hp_X]/1 mL; SULFUR 9 [hp_C]/1 mL; COMFREY ROOT 6 [hp_X]/1 mL; VERATRUM ALBUM ROOT 30 [hp_X]/1 mL; VERBASCUM THAPSUS 1 [hp_X]/1 mL; ARSENIC TRIOXIDE 15 [hp_X]/1 mL; BELLIS PERENNIS 12 [hp_X]/1 mL; CALENDULA OFFICINALIS FLOWERING TOP 9 [hp_X]/1 mL; MATRICARIA CHAMOMILLA WHOLE 8 [hp_X]/1 mL; EUPATORIUM PERFOLIATUM FLOWERING TOP 8 [hp_X]/1 mL; FERROSOFERRIC PHOSPHATE 15 [hp_X]/1 mL; HAMAMELIS VIRGINIANA ROOT BARK/STEM BARK 3 [hp_X]/1 mL; HYPERICUM PERFORATUM 6 [hp_X]/1 mL; IMPATIENS GLANDULIFERA FLOWER 30 [hp_X]/1 mL; ACHILLEA MILLEFOLIUM 3 [hp_X]/1 mL; ACONITUM NAPELLUS 30 [hp_X]/1 mL; CLEMATIS VITALBA FLOWER 30 [hp_X]/1 mL; SOLANUM DULCAMARA WHOLE 8 [hp_X]/1 mL
INACTIVE INGREDIENTS: ALCOHOL; WATER

B21

Active Ingredients
Aconitum Napellus | 9X 12X 30X
Apis Mellifica | 6X 9X 12X
Arnica Montana | 6X 9X 12X 30X
Arsenicum Album | 9X 12X 15X
Belladonna | 6X 9X 12X 30X
Bellis Perennis | 6X 9X 12X
Bryonia | 6X 9X 12X
Calendula Officinalis | 3X 6X 9X
Chamomilla | 4X 6X 8X
Cherry Plum Flower | 9X 12X 30X
Clematis Vitalba Flower | 9X 12X 30X
Colocynthis | 4X 6X 8X
Dulcamara Lignosa Whole | 4X 6X 8X
Echinacea Angustifolia | 6X
Echinacea Purpurea | 6X
Eupatorium Perfoliatum | 4X 6X 8X
Ferrum Phosphoricum | 12X 15X
Hamamelis Virginiana | 3X
Histaminum Hydrochloricum | 6X 9X 12X
Hypericum Perforatum | 3X 6X
Impatiens Glandulifera Flower | 9X 12X 30X
Ledum Palustre | 1X
Mentha Piperita | 1X
Millefolium | 3X
Plantago Major | 1X
Pyrenees Star Of Bethlehem Flowering Top | 9X 12X 30X
Rhus Toxicodendron | 6X 9X 12X
Rockrose Flower | 9X 12X 30X
Sulphur | 3C 6C 9C
Symphytum Officinale | 3X 6X
Veratrum Album | 12X 30X
Verbascum Thapsus | 1X

INDICATIONS AND USAGE

Uses:

For temporary relief of minor:

inflammation*

pain*

common cold/flu*

bruises*

sore throat*

muscle aches*

*Claims based on traditional homeopathic practice, not accepted medical evidence. Not FDA evaluated.

Warnings:

PREGNANCY OR BREAST FEEDING

If pregnant or breastfeeding, ask a health professional before use.

Do not use if clear seal over the cap is broken or missing.

Keep out of reach of children. In case of overdose, get medical help or contact a Poison Control Center right away.

Stop use and ask a doctor if inflammation, pain, common cold/flu, bruises, sore throat, muscle aches, or other symptoms do not improve within 7 days or are accompanied by fever.

Directions:

Adults & children ages 12 years and over: Take 2-3 sprays orally, or topically as directed by your healthcare professional. Consult a physician for use in children under 12 years of age.

Inactive Ingredients

alcohol (20% by volume), distilled water

Distributed by Apex Energetics. Questions?

16592 Hale Ave., Irvine, CA 92606, USA

PACKAGE LABEL

FUTUREPLEX® B21

ANTITOX®

ACUTE RESCUE™

SPRAY-XL

Homeopathic Formula

Inflammation* Pain*

Common Cold/Flu*

2 fl oz (60 mL)

Alcohol 20% by Volume